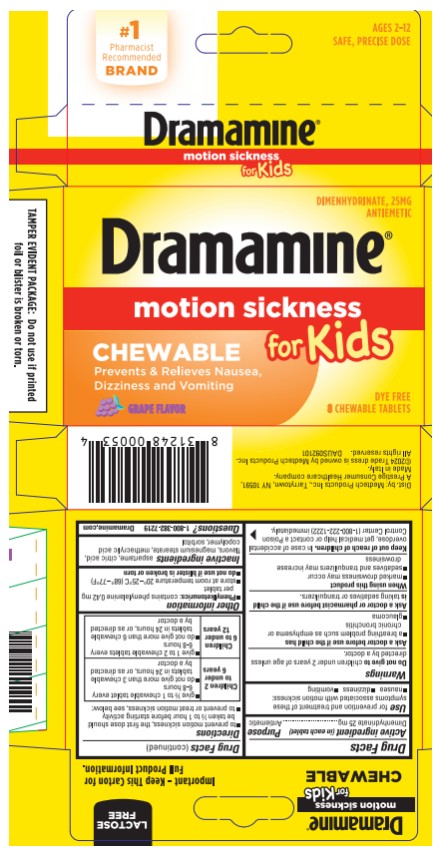 DRUG LABEL: Dramamine for Kids
NDC: 63029-908 | Form: TABLET, CHEWABLE
Manufacturer: Medtech Products Inc.
Category: otc | Type: HUMAN OTC DRUG LABEL
Date: 20250212

ACTIVE INGREDIENTS: DIMENHYDRINATE 25 mg/1 1
INACTIVE INGREDIENTS: ASPARTAME; ANHYDROUS CITRIC ACID; GRAPE; MAGNESIUM STEARATE; METHACRYLIC ACID - METHYL METHACRYLATE COPOLYMER (1:1); SORBITOL

Dramamine Chewable Tablets for Kids- Grape

Drug Facts

Active ingredient (in each tablet)

Dimenhydrinate 25mg

Purpose

Antiemetic

Use

for prevention and treatment of these symptoms associated with motion sickness:

- nausea
- dizziness
- vomiting

Warnings

Do not give to children under 2 years of age unless directed by a doctor.

Ask a doctor before use if the child has

- a breathing problem such as emphysema or chronic bronchitis
- glaucoma

Ask a doctor before use if the child is

taking sedatives or tranquilizers

When using this product

- marked drowsiness may occur
- sedatives, and tranquilizers may increase drowsiness

Keep out of reach of children.

In case of accidental overdose, get medical help or contact a Poison Control Center (1-800-222-1222) immediately.

Directions

- To prevent motion sickness, the first dose should be taken ½ to 1 hour before starting activity
- To prevent or treat motion sickness see below:

- Children 2 to under 6 years Give ½ to 1 chewable tablet every 6-8 hours

- Do not give more than 3 chewable tablets in 24 hours or as directed by a doctor

Children 6 to 12 years

- Give 1 to 2 chewable tablets every 6-8 hours
- Do not give more than 6 chewable tablets in 24 hours, or as directed by a doctor

Other information

- Phenylketonurics: contains phenylalanine 0.42 mg per tablet
- Store at room temperature 20◦-25◦C (68◦-77◦F)
- Do not use if blister is broken or torn

Inactive ingredients

aspartame, citric acid, flavors, magnesium stearate, methacrylic acid copolymer, sorbitol

Questions?

1-800-382-7219 Dramamine.com

Dist. by Medtech Products Inc., Tarrytown, NY 10591
A Prestige Consumer Healthcare company.
Made in Italy
©2024 Trade dress is owned by Medtech Products Inc. All rights reserved.
DAUS092101

Principal display panel

Dramamine®
motion sickness
for Kids
CHEWABLE
DYE FREE
8 CHEWABLE TABLETS
GRAPE FLAVOR